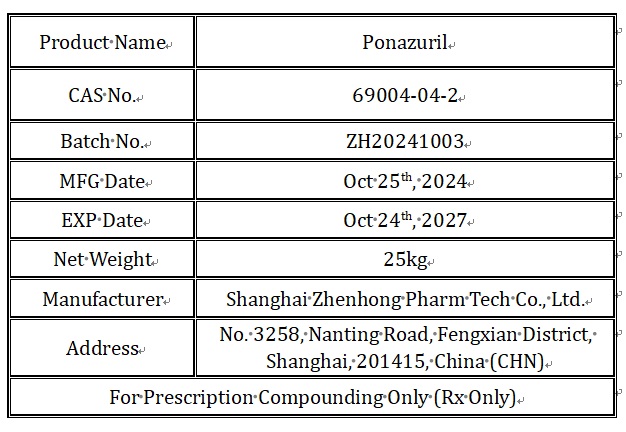 DRUG LABEL: Ponazuril
NDC: 86228-001 | Form: POWDER
Manufacturer: Shanghai Zhenhong Pharm Tech Co., Ltd.
Category: other | Type: BULK INGREDIENT - ANIMAL DRUG
Date: 20250428

ACTIVE INGREDIENTS: PONAZURIL 1 kg/1 kg

86228-001